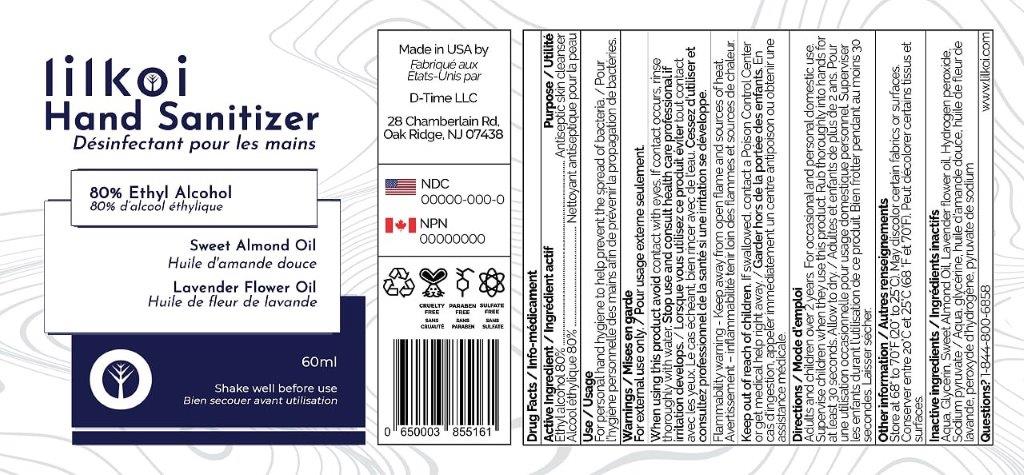 DRUG LABEL: lilkoi Hand Sanitizer
NDC: 75306-007 | Form: SPRAY
Manufacturer: D-Time Limited Liability Company
Category: otc | Type: HUMAN OTC DRUG LABEL
Date: 20211102

ACTIVE INGREDIENTS: ALCOHOL 80 mL/100 mL
INACTIVE INGREDIENTS: WATER; GLYCERIN; ALMOND OIL; LAVENDER OIL; HYDROGEN PEROXIDE; SODIUM PYRUVATE

Active Ingredient

Ethyl Alcohol 80%

Purpose

Antiseptic skin cleanser

Uses

For personal hand hygiene to help prevent the spread of bacteria.

Warnings

For external use only.

Flammable. Keep away from open flame and sources of heat.

When using this product avoid contact with eyes. If contact occurs, rinse thoroughly with water.

Stop use and consult a healthcare professional if irritation develops.

Keep out of reach of children.If swallowed, contact a Poison Control Center or get medical help right away.

Directions

Adults and children over 2 years: For occasional and personal domestic use Supervise children when they use this product ∙ Spray onto hands and rub thoroughly for at least 30 seconds. Allow to dry.

Other information

Store at 68° to 70° F (20° to 25° C).

May discolor certain fabrics or surfaces.

Questions? 1-844-800-6858

Inactive ingredients

Water, Glycerin, Sweet almond oil, Lavender Flower Oil, Hydrogen Peroxide, Sodium pyruvate.